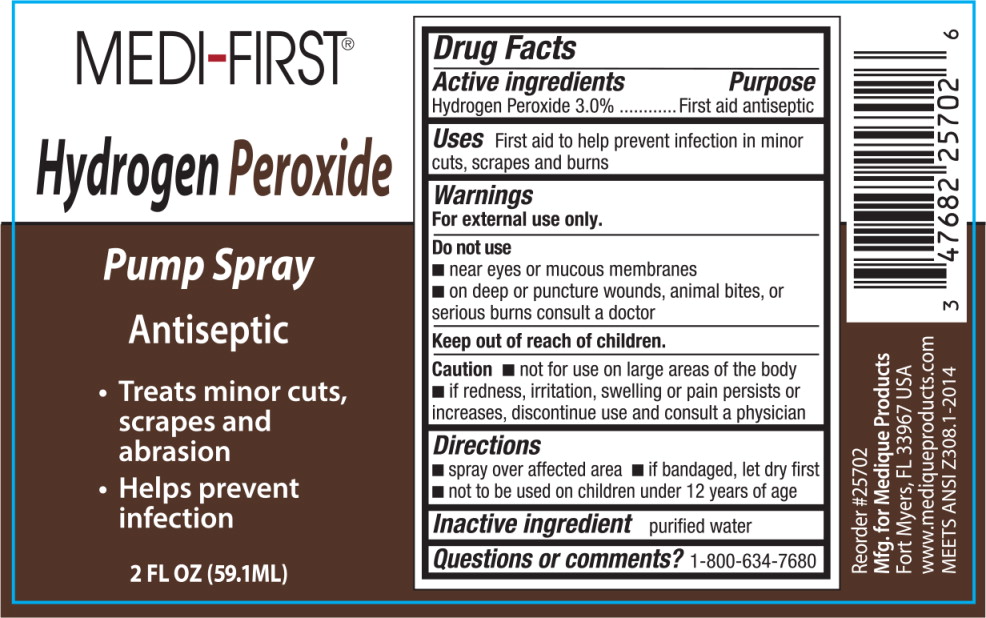 DRUG LABEL: MediFirst Hydrogen Peroxide
NDC: 47682-257 | Form: SPRAY
Manufacturer: Unifirst First Aid Corporation
Category: otc | Type: HUMAN OTC DRUG LABEL
Date: 20250908

ACTIVE INGREDIENTS: HYDROGEN PEROXIDE 43.275 g/1 L
INACTIVE INGREDIENTS: WATER

Medi-First Hydrogen Peroxide Spray

Drug Facts

Active Ingredients

Hydrogen Peroxide 3.0%

Purpose

First aid antiseptic

Uses

First aid to help prevent infection in minor cuts, scrapes and burns

Warnings

For external use only.

Do not use

- near eyes or mucous membranes
- on deep or puncture wounds, animal bites, or serious burns consult a doctor

Keep out of reach of children.

Caution

- not for use on large areas of the body
- if redness, irritation, swelling or pain persists or increases, discontinue use and consult a physician

Directions

- spray over affected area
- if bandaged, let dry first
- not to be used on children under 12 years of age

Inactive ingredient

purified water

Questions or Comments?

1-800-634-7680

Medi-First Hydrogen Peroxide Spray Label

MEDI-FIRST®

Hydrogen Peroxide

Pump Spray

Antiseptic

- Treats minor cuts, scrapes and abrasion
- Helps prevent infection

2 FL OZ (59.1ML)